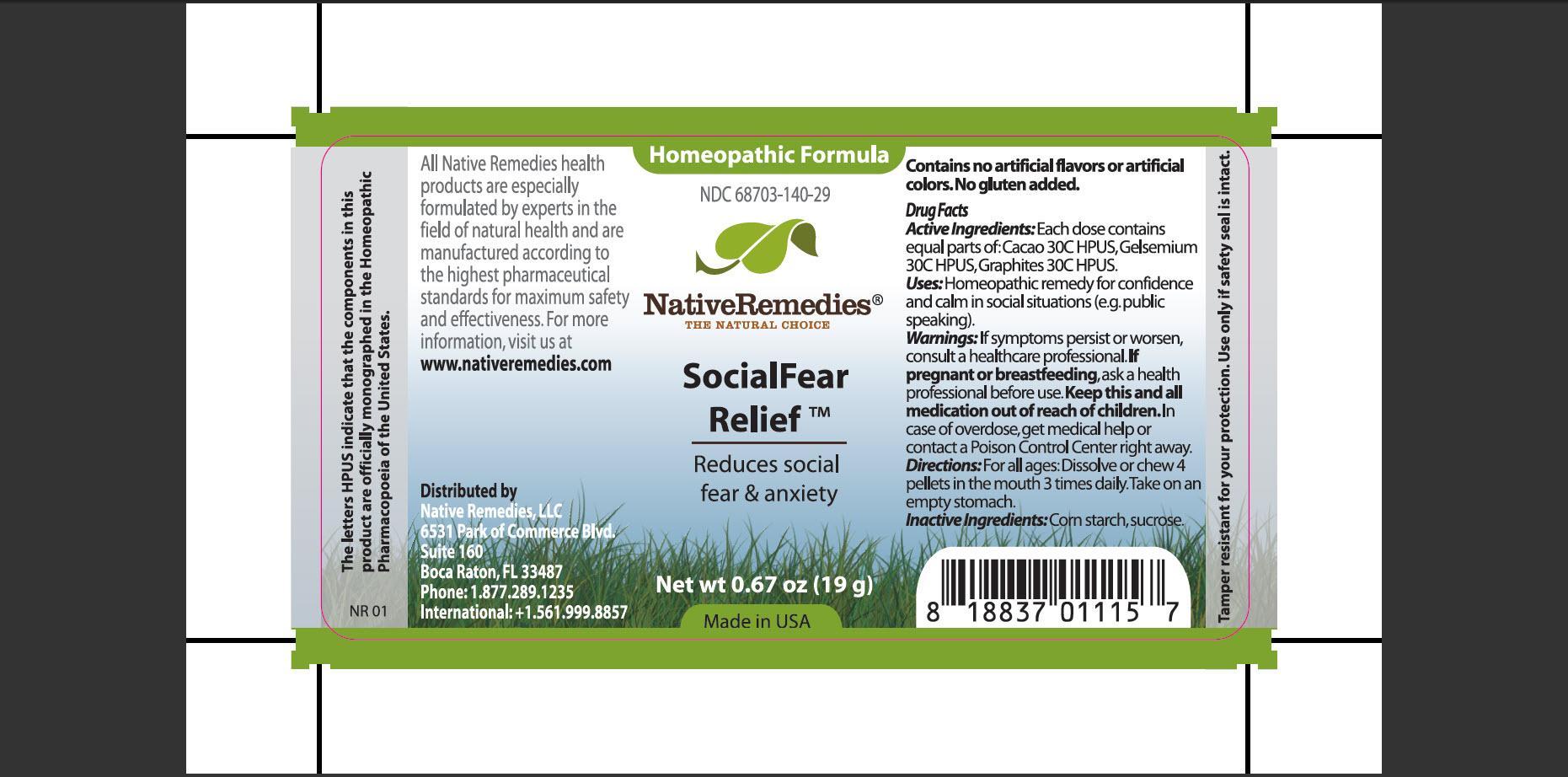 DRUG LABEL: SocialFear Relief
NDC: 68703-140 | Form: PELLET
Manufacturer: Native Remedies, LLC
Category: homeopathic | Type: HUMAN OTC DRUG LABEL
Date: 20130820

ACTIVE INGREDIENTS: COCOA 30 [hp_C]/19 g; GELSEMIUM SEMPERVIRENS ROOT 30 [hp_C]/19 g; GRAPHITE 30 [hp_C]/19 g
INACTIVE INGREDIENTS: STARCH, CORN; SUCROSE

SocialFear Relief

PURPOSE

Reduces social fear and anxiety

Drug Facts
Active Ingredients:Each dose contains equal parts of : Cacao 30C HPUS, Gelsemium 30C HPUS, Graphites 30C HPUS

INDICATIONS AND USAGE

Uses: Homeopathic remedy for confidence and calm in social situations (e.g. public speaking)

WARNINGS

Warnings:If symptoms persist or worsen, consult a healthcare professional

PREGNANCY OR BREAST FEEDING

If pregnant or breastfeeding, ask a health professional before use

KEEP OUT OF REACH OF CHILDREN

Keep this and all medication out of reach of children

OVERDOSAGE

In case of overdose, get medical help or contact a Poison Control Center right away

DOSAGE AND ADMINISTRATION

Directions: For all ages: Dissolve or chew 4 pellets in the mouth 3 times daily. Take on an empty stomach

Inactive Ingredients: Corn starch, sucrose

PATIENT COUNSELING INFORMATION

The letters HPUS indicate that the components in this product are officially monographed in the Homeopathic Pharmacopoeia of the United States

All Native Remedies health products are especially formulated by experts in the field of natural health and are manufactured according to the highest pharmaceutical standards for maximum safety and effectiveness. For more information, visit us at www.nativeremedies.com

Distributed by
Native Remedies, LLC
6531 Park of Commerce Blvd.
Suite 160
Boca Raton, FL 33487
Phone: 1.877.289.1235
International: +1.561.999.8857

Contains no artificial flavors or artificial colors. No gluten added

STORAGE AND HANDLING

Tamper resistant for your protection. Use only if safety seal is intact